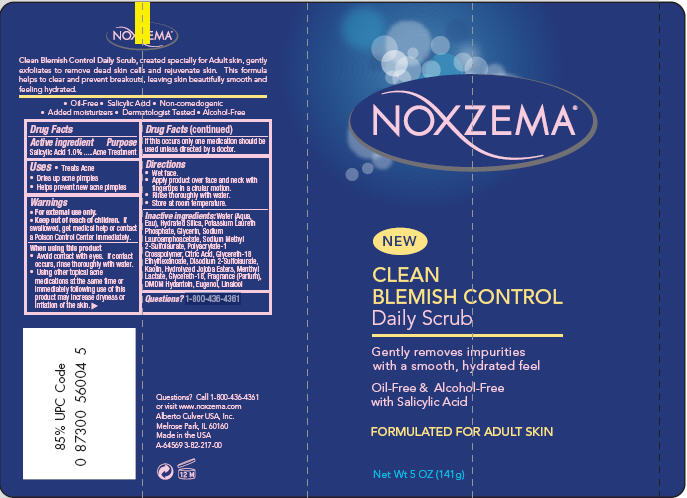 DRUG LABEL: Noxzema
NDC: 12488-1200 | Form: SOAP
Manufacturer: Alberto-Culver USA Inc. 
Category: otc | Type: HUMAN OTC DRUG LABEL
Date: 20091217

ACTIVE INGREDIENTS: Salicylic Acid 0.01 g/1 g
INACTIVE INGREDIENTS: Water; Glycerin; Kaolin; Citric Acid Monohydrate; Menthyl Lactate

NOXZEMA®

Drug Facts

Active ingredient

Salicylic Acid 1.0%

Purpose

Acne Treatment

Uses

- Treats Acne
- Dries up acne pimples
- Helps prevent new acne pimples

Warnings

- For external use only.
- Keep out of reach of children. If swallowed, get medical help or contact a Poison Control Center immediately.

When using this product

- Avoid contact with eyes. If contact occurs, rinse thoroughly with water.
- Using other topical acne medications at the same time or immediately following use of this product may increase dryness or irritation of the skin.
  If this occurs only one medication should be used unless directed by a doctor.

Directions

- Wet face.
- Apply product over face and neck with fingertips in a cirular motion.
- Rinse thoroughly with water.
- Store at room temperature.

Inactive ingredients

Water (Aqua, Eau), Hydrated Silica, Potassium Laureth Phosphate, Glycerin, Sodium Lauroamphoacetate, Sodium Methyl 2-Sulfolaurate, Polyacrylate-1 Crosspolymer, Citric Acid, Glycereth-18 Ethylhexanoate, Disodium 2-Sulfolaurate, Kaolin, Hydrolyzed Jojoba Esters, Menthyl Lactate, Glycereth-18, Fragrance (Parfum), DMDM Hydantoin, Eugenol, Linalool

Questions?

1-800-436-4361

PRINCIPAL DISPLAY PANEL - 141 gram Tube

NOXZEMA®

NEW

CLEAN
BLEMISH CONTROL
Daily Scrub

Gently removes impurities
with a smooth, hydrated feel

Oil-Free & Alcohol-Free
with Salicylic Acid

FORMULATED FOR ADULT SKIN

Net Wt 5 OZ (141g)